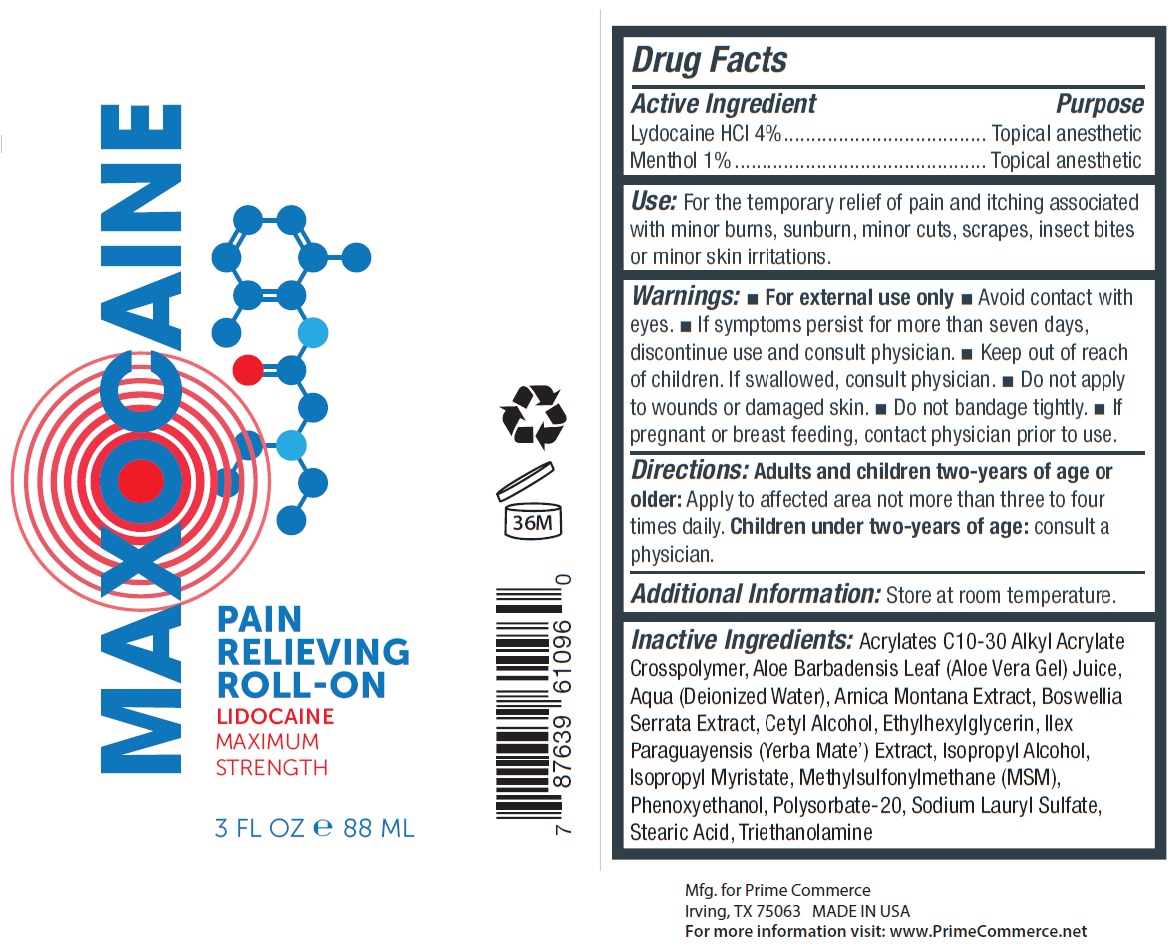 DRUG LABEL: MAXOCAINE PAIN RELIEVING ROLL-ON
NDC: 72188-170 | Form: LIQUID
Manufacturer: Prime Commerce, LLC
Category: otc | Type: HUMAN OTC DRUG LABEL
Date: 20231111

ACTIVE INGREDIENTS: LIDOCAINE HYDROCHLORIDE 40 mg/1 mL; MENTHOL 10 mg/1 mL
INACTIVE INGREDIENTS: ALOE VERA LEAF; WATER; ARNICA MONTANA; INDIAN FRANKINCENSE; CETYL ALCOHOL; ETHYLHEXYLGLYCERIN; ILEX PARAGUARIENSIS LEAF; ISOPROPYL ALCOHOL; ISOPROPYL MYRISTATE; DIMETHYL SULFONE; PHENOXYETHANOL; POLYSORBATE 20; SODIUM LAURYL SULFATE; STEARIC ACID; TROLAMINE

MAXOCAINE PAIN RELIEVING ROLL-ON

Active Ingredient

Lydocaine HCL 4%

Menthol 1%

Purpose

Topical anesthetic

Use:

For the temporary relief of pain and itching associated with minor burns, sunburn, minor cuts, scrapes, insect bites or minor skin irritations.

Warnings:

- For external use only
- Avoid contact with eyes.
- If symptoms persist for more than seven days, discontinue use and consult physician.

Keep out of reach of children.

If swallowed, consult physician.

Do not apply

- to wounds or damaged skin.
- Do not bandage tightly.

If pregnant or breast feeding,

contact physician prior to use.

Directions:

Apply to affected area not more than three to four times daily. consult a physician. Adults and children two-years of age or older:Chinldren under two-years of age:

Additional Information:

Store at room temperature.

Inactive Information:

Acrylates C10-30 Alkyl Acrylate Crosspolymer, Aloe Barbadensis Leaf (Aloe Vera Gel) Juice, Aqua (Deionized Water), Arnica Montana Extract, Boswellia Serrata Extract, Cetyl Alcohol, Ethylhexylglycerin, Ilex Paraguayensis (Yerba Mate') Extract, Isopropyl Alcohol, Isopropyl Myristate, Methylsulfonylmethane (MSM), Phenoxyethanol, Polysorbate-20, Sodium Lauryl Sulfate, Stearic Acid, Triethanolamine